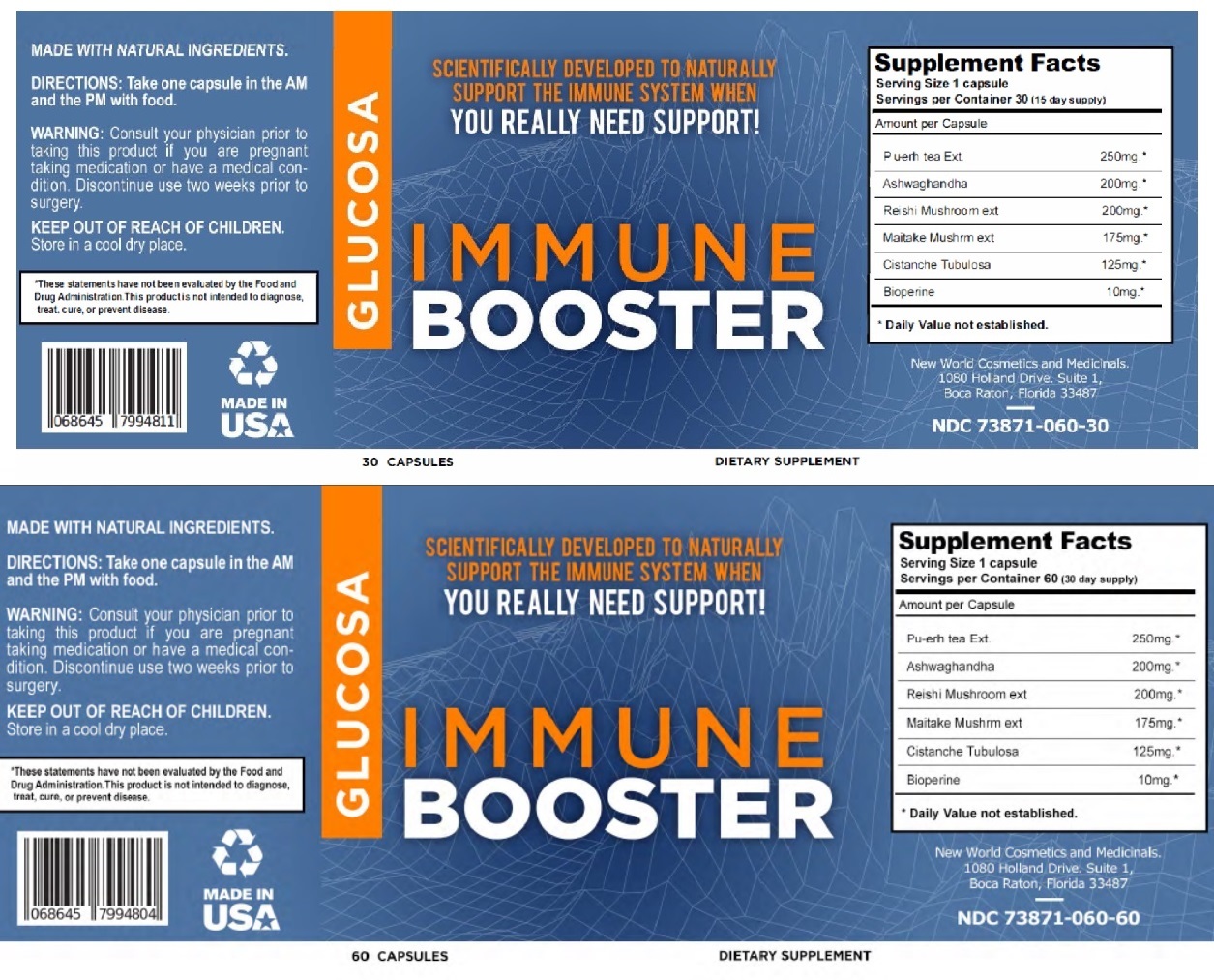 DRUG LABEL: GLUCOSA IMMUNE BOOSTER
NDC: 73871-060 | Form: CAPSULE
Manufacturer: New World Holdings, Inc.
Category: other | Type: DIETARY SUPPLEMENT
Date: 20200506

ACTIVE INGREDIENTS: GREEN TEA LEAF 250 mg/1 1; WITHANIA SOMNIFERA ROOT 200 mg/1 1; REISHI 200 mg/1 1; MAITAKE 175 mg/1 1; CISTANCHE TINCTORIA STEM 125 mg/1 1; PIPERINE 10 mg/1 1

GLUCOSA IMMUNE BOOSTER

STATEMENT OF IDENTITY

Supplement Facts
Serving Size 1 capsule
Servings per Container 60 (30 day supply)
Amount per Capsule
Pu-erh tea Ext. | 250mg.*
Ashwagandha | 200mg.*
Reishi Mushroom ext | 200mg.*
Maitake Mushroom ext | 175mg.*
Cistanche Tubulosa | 125mg.*
Bioperine | 10mg.*
* Daily Value not established.

DOSAGE AND ADMINISTRATION

DIRECTIONS: Take one capsule in the AM and the PM with food.

WARNINGS

WARNING: Consult your physician prior to taking this product if you are pregnant taking medication or have a medical condition. Discontinue use two weeks prior to surgery.

KEEP OUT OF REACH OF CHILDREN.

Store in a cool dry place.

HEALTH CLAIM

SCIENTIFICALLY DEVELOPED TO NATURALLY SUPPORT THE IMMUNE SYSTEM WHEN YOU REALLY NEED SUPPORT!
MADE WITH NATURAL INGREDIENTS.

*These statements have not been evaluated by the Food and Drug Administration. This product is not intended to diagnose, treat, cure, or prevent disease.

MADE IN USA

DIETARY SUPPLEMENT

New World Cosmetics and Medicinals.
1080 Holland Drive. Suite 1,
Boca Raton, Florida 33487